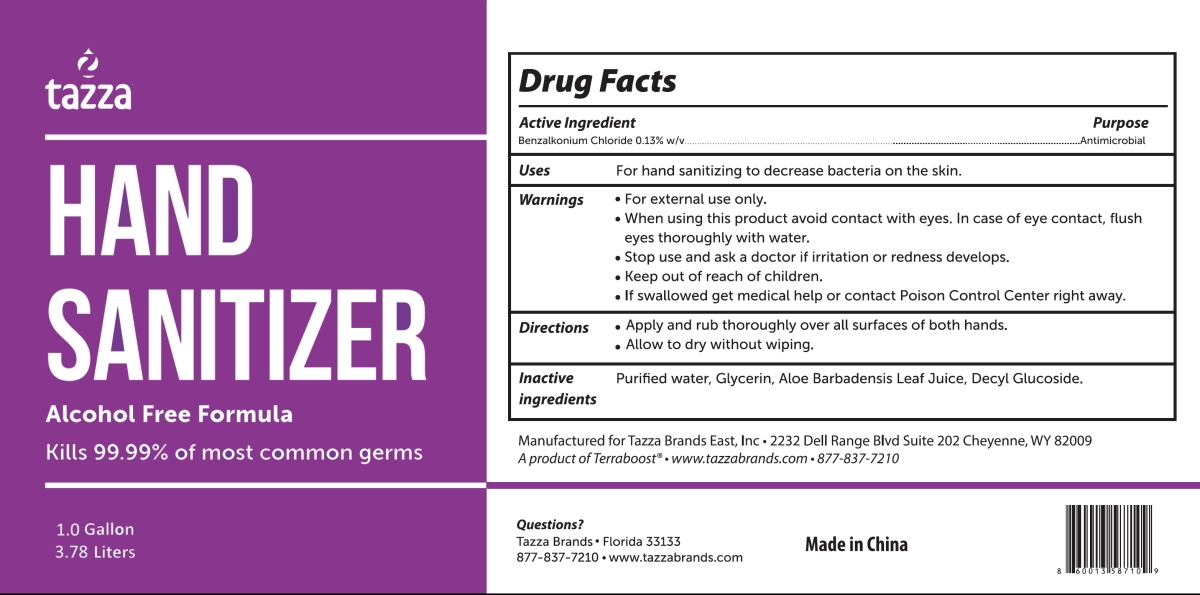 DRUG LABEL: tazza HAND SANITIZER
NDC: 76370-0032 | Form: LIQUID
Manufacturer: Tazza Brands East Inc.
Category: otc | Type: HUMAN OTC DRUG LABEL
Date: 20251224

ACTIVE INGREDIENTS: BENZALKONIUM CHLORIDE 0.13 g/0.1 L
INACTIVE INGREDIENTS: GLYCERIN; ALOE BARBADENSIS LEAF JUICE; DECYL GLUCOSIDE; WATER

76370-0032 tazza HAND SANITIZER

Active Ingredient

Benzalkonium Chloride 0.13% w/v

Purpose

Antimicrobial

INDICATIONS AND USAGE

Uses For hand sanitizing to decrease bacteria on the skin.

Warnings

· For external use only.

· When using this product avoid contact with eyes. In case of eye contact, flush eyes thoroughly with water.

· Stop use and ask a doctor if irritation or redness develops.

· Keep out of reach of children.

· If swallowed get medical help or contact Poison Control Center right away.

· When using this product avoid contact with eyes. In case of eye contact, flush eyes thoroughly with water.

· Stop use and ask a doctor if irritation or redness develops.

· Keep out of reach of children.

Directions

· Apply and rub thoroughly over all surfaces of both hands.

· Allow to dry without wiping.

Inactive Ingredients

Purified Water, Glycerin, Aloe Barbadensis Leaf Juice, Decyl Glucoside.

PACKAGE LABEL

1.0 Gallon
3.78 Liters
NDC: 76370-0032-0